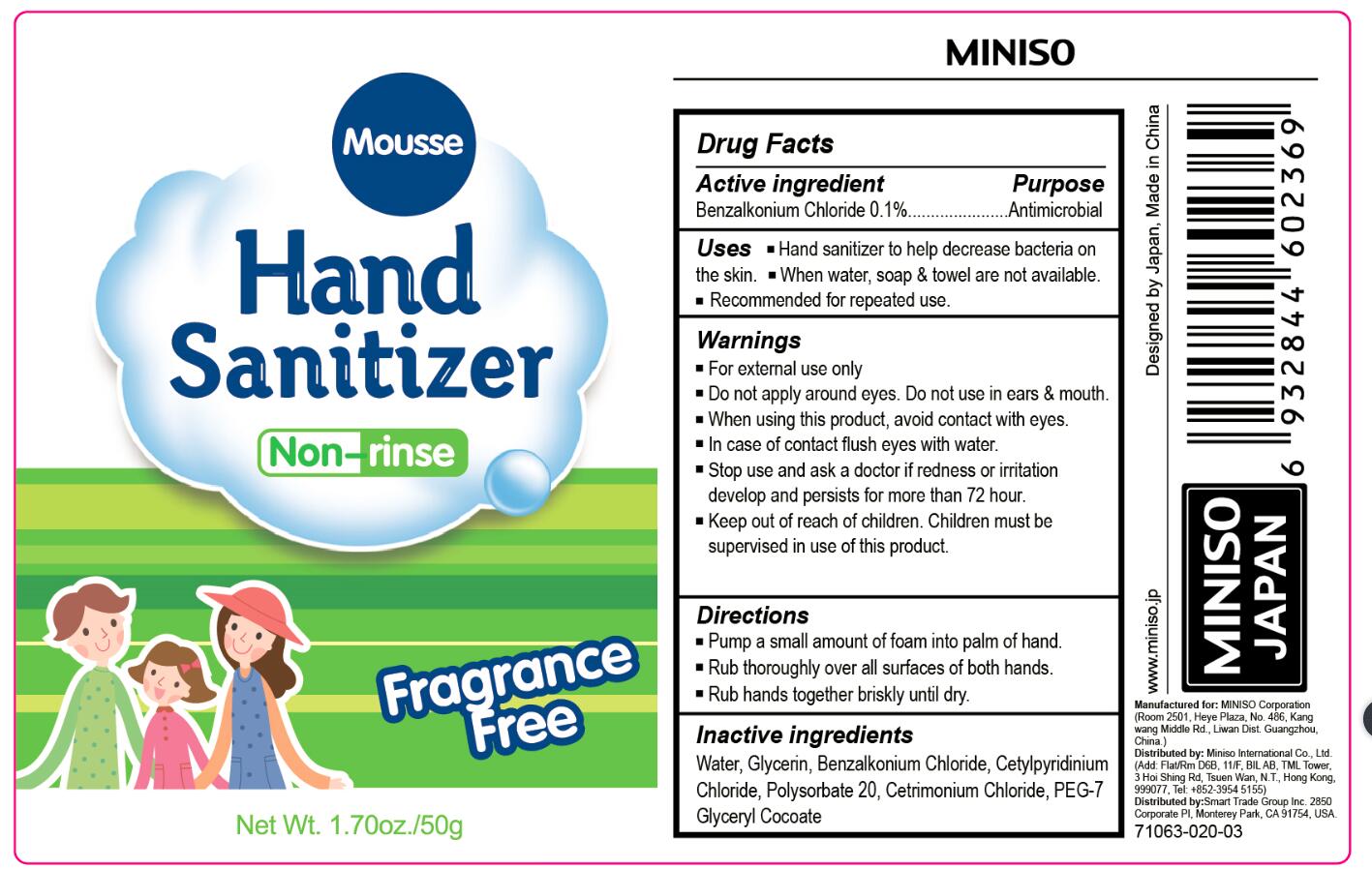 DRUG LABEL: Mousse Non-rinse Hand Sanitizer(Fragrance Free / Grapefruit)
NDC: 61312-011 | Form: GEL
Manufacturer: Hangzhou  Guoguang  Touring  Commodity  Co., Ltd.
Category: otc | Type: HUMAN OTC DRUG LABEL
Date: 20180109

ACTIVE INGREDIENTS: BENZALKONIUM CHLORIDE 0.1 g/100 g
INACTIVE INGREDIENTS: ALPHA-TOCOPHEROL ACETATE; WATER; PEG-7 GLYCERYL COCOATE; GLYCERIN; POLYSORBATE 20; CETRIMONIUM CHLORIDE; CETYLPYRIDINIUM CHLORIDE

61312-011 Mousse Non-rinse Hand Sanitizer(Fragrance Free / Grapefruit)

Active Ingredient

BENZALKONIUM CHLORIDE 0.1%

Purpose

Antimicrobial

Use

Hand sanitizer to help decrease bacteria on the skin.

when water,soap &towel are note available.

recommended for repeated use.

Warning

For external use only
Flammable
Keep away from fire or flame
Do not apply around eyes,do not use in ears&mouth.

when using this product,avoid contact with eyes,

In case of contact flush eyes with water

Stop use and ask a doctor if redness or irritation develop and persist for more than 72 hour

Keep out of reach of children ,children must be supervised in use of this product.

Directions

pump as needed into your palms and thoroughly spread on both hands,rub into skin until dry.

INACTIVE INGREDIENT

Water,Glycerin,Aloe Barbadensis Leaf Juice, Carbomer,Fragrance,Triethanolamine,Tocopheryl Acetate,